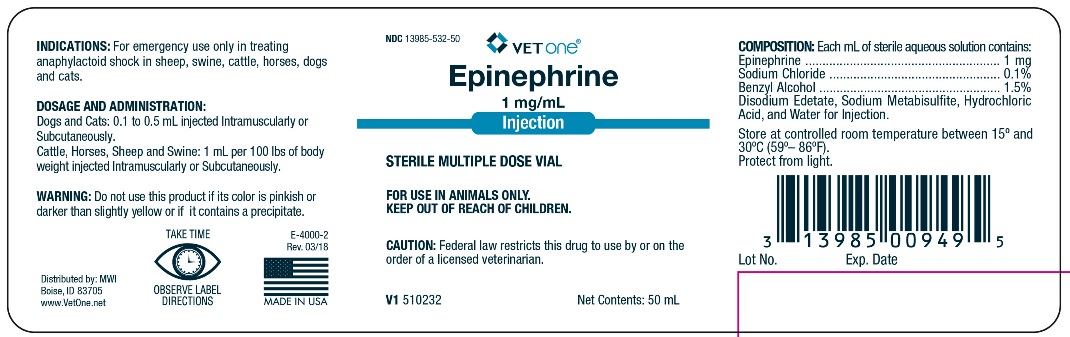 DRUG LABEL: EPINEPHRINE
NDC: 13985-532 | Form: INJECTION
Manufacturer: MWI/VetOne
Category: animal | Type: PRESCRIPTION ANIMAL DRUG LABEL
Date: 20250304

ACTIVE INGREDIENTS: EPINEPHRINE 1 mg/1 mL
INACTIVE INGREDIENTS: EDETATE DISODIUM

EPINEPHRINE INJECTION 1mg/mL

INDICATIONS AND USAGE

STERILE MULTIPLE DOSE VIAL

FOR USE IN ANIMALS ONLY

KEEP OUT OF REACH OF CHILDREN

CAUTION: Federal law restricts this drug to use by or on the order of a licensed veterinarian.

INDICATIONS:

For emergency use only in treating anaphylactoid shock in sheep, swine, horses, dogs, and cats.

DOSAGE AND ADMINISTRATION

Dogs and Cats: 0.1 to 0.5 mL Injected Intramuscularly or Subcutaneously.
Cattle, Horses, Sheep and Swine: 1 mL per 100 lbs of body weight injected Intramuscularly or Subcutaneously.

WARNING:

Do not use this product if its color is pinkish or darker than slightly yellow or it contains a precipitate.

COMPOSITION

Each mL of sterile aqueous solution contains:
Epinephrine ................................. 1 mg
Sodium Chloride .......................... 0.1%
Benzyl Alcohol ............................ 1.5%
Disodium Edetate, Sodium Metabisulfite, Hydrochloric Acid, and Water for Injection

STORAGE AND HANDLING

Store at controlled room temperature between 15o and 30o (59o - 86o F).

Protect from light.